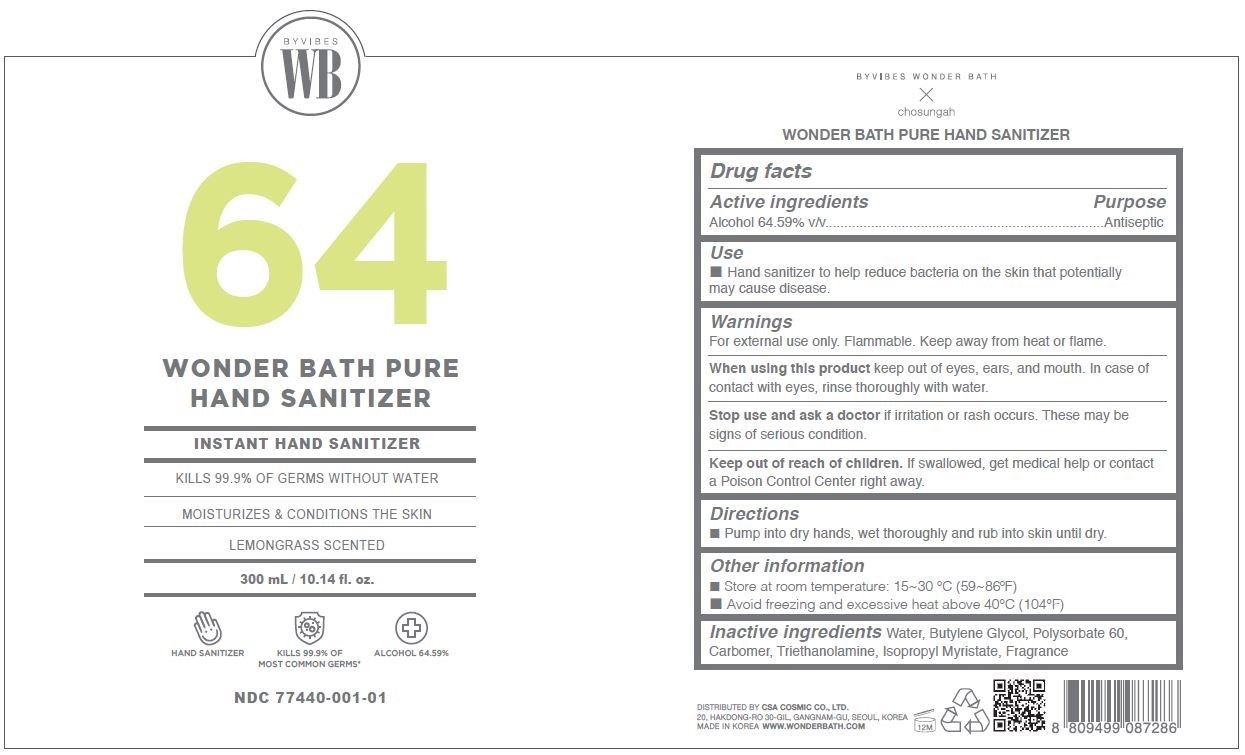 DRUG LABEL: WONDER BATH PURE HAND SANITIZER
NDC: 77440-001 | Form: GEL
Manufacturer: CSA COSMIC CO., LTD.
Category: otc | Type: HUMAN OTC DRUG LABEL
Date: 20200604

ACTIVE INGREDIENTS: ALCOHOL 64.59 mL/100 mL
INACTIVE INGREDIENTS: BUTYLENE GLYCOL; POLYSORBATE 60; WATER; TROLAMINE; CARBOMER HOMOPOLYMER, UNSPECIFIED TYPE; ISOPROPYL MYRISTATE

Active Ingredient(s)

Alcohol 64.59% v/v.

Purpose

Antiseptic

Use

Hand Sanitizer to help reduce bacteria on the skin that potentially may cause disease.

Warnings

For external use only. Flammable. Keep away from heat or flame.

When using this product keep out of eyes, ears, and mouth. In case of contact with eyes, rinse thoroughly with water.

Stop use and ask a doctor if irritation or rash occurs. These may be signs of a serious condition.

Keep out of reach of children. If swallowed, get medical help or contact a Poison Control Center right away.

Directions

- Pump into dry hands, wet thoroughly and rub into skin until dry.

Other information

- Store between 15-30˚C (59-86˚F)
- Avoid freezing and excessive heat above 40˚C (104˚F)

Inactive ingredients

Water, Butylene Glycol, Polysorbate 60, Carbomer, Triethanolamine, Isopropyl Myristate, Fragrance